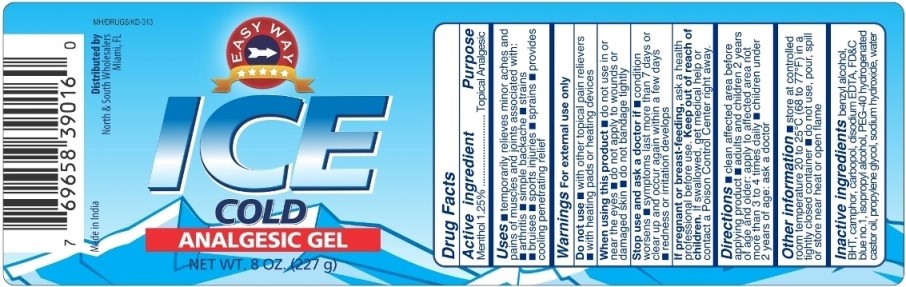 DRUG LABEL: Ice Cold Analgesic
NDC: 70201-005 | Form: GEL
Manufacturer: North & South Wholesalers LLC
Category: otc | Type: HUMAN OTC DRUG LABEL
Date: 20180819

ACTIVE INGREDIENTS: MENTHOL 1.25 g/100 g
INACTIVE INGREDIENTS: BENZYL ALCOHOL; BUTYLATED HYDROXYTOLUENE; CAMPHOR (SYNTHETIC); CARBOMER HOMOPOLYMER TYPE B (ALLYL SUCROSE CROSSLINKED); EDETATE DISODIUM; FD&C BLUE NO. 1; ISOPROPYL ALCOHOL; POLYOXYL 40 HYDROGENATED CASTOR OIL; PROPYLENE GLYCOL; SODIUM HYDROXIDE; WATER

Ice Cold Analgesic Gel

Active Ingredient

Menthol 1.25%

Purpose

Topical Analgesic

Uses

- temporarily relieves minor aches and pains of muscles and joints associated with:
- arthritis
- simple backache
- strains
- bruises
- sports injuries
- sprains
- provides cooling penetrating relife

Warnings

For external use only

Do not use

- with other topical pain relievers
- with heating pads or heating devices

When using this product

- do not use in or near the eyes
- do not apply to wounds or damaged skin
- do not bandage tightly

Stop use and ask a doctor if

- condition worsens
- symptoms last more than 7 days or clean up and occur again within a few days
- redness or irritation develops

PREGNANCY OR BREAST FEEDING

If pregnant or breast-feeding, ask a health professional before use

Keep out of the reach of children

If swallowed, get medical help or contact a Poison Control Center right away

Directions

- clean affected area before applying product
- adults and children 2 years of age and older: apply to affected area not more than 3 to 4 times daily
- children under 2 years of age: ask a doctor

Other information

- store at controlled room temperature 20 to 25°C (68 to 77°F) in a tightly closed container.
- do not use, pour, spill or store near heat or open flame.

Inactive Ingredients

benzyl alcohol, BHT, camphor, carbopol, disodium EDTA, FD&C blue no.1, isopropyl alcohol, PEG-40 hydrogenated castor oil, propylene glycol, sodium hydroxide, water.

PACKAGE LABEL

PRINCIPAL DISPLAY PANEL

ICE COLD ANALGESIC GEL

Topical Analgesic

NET WT.8 OZ (227g)